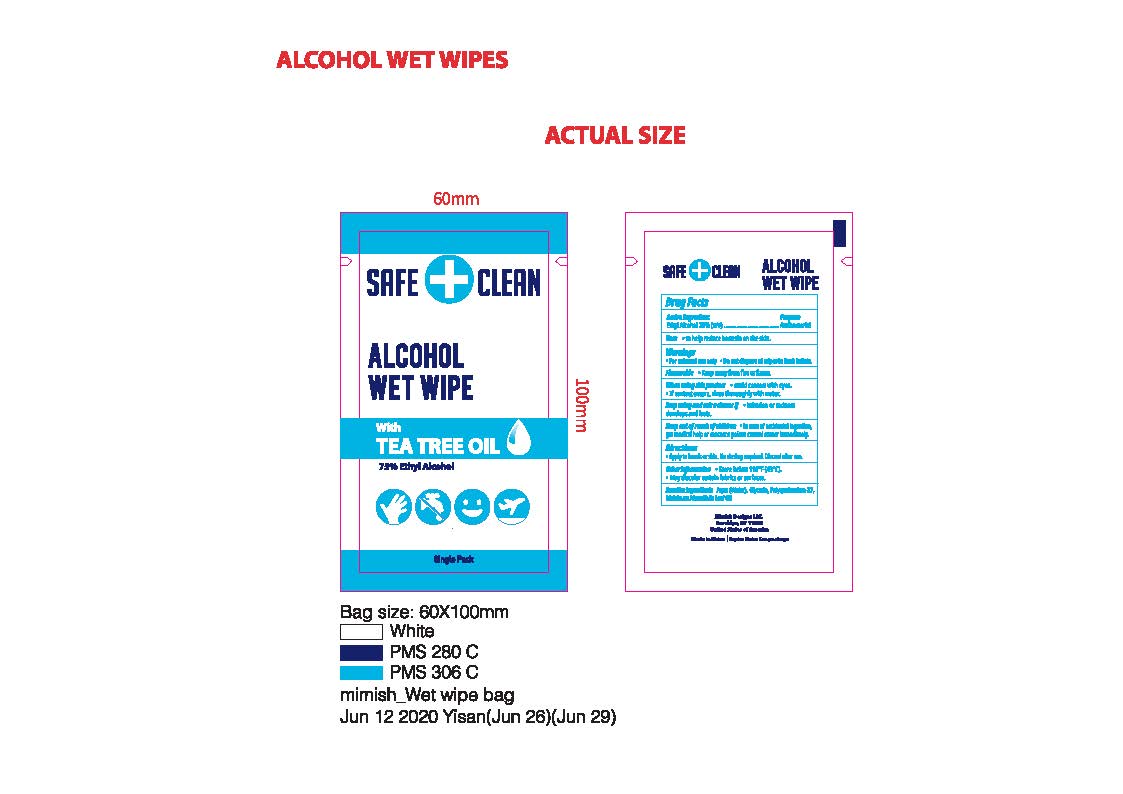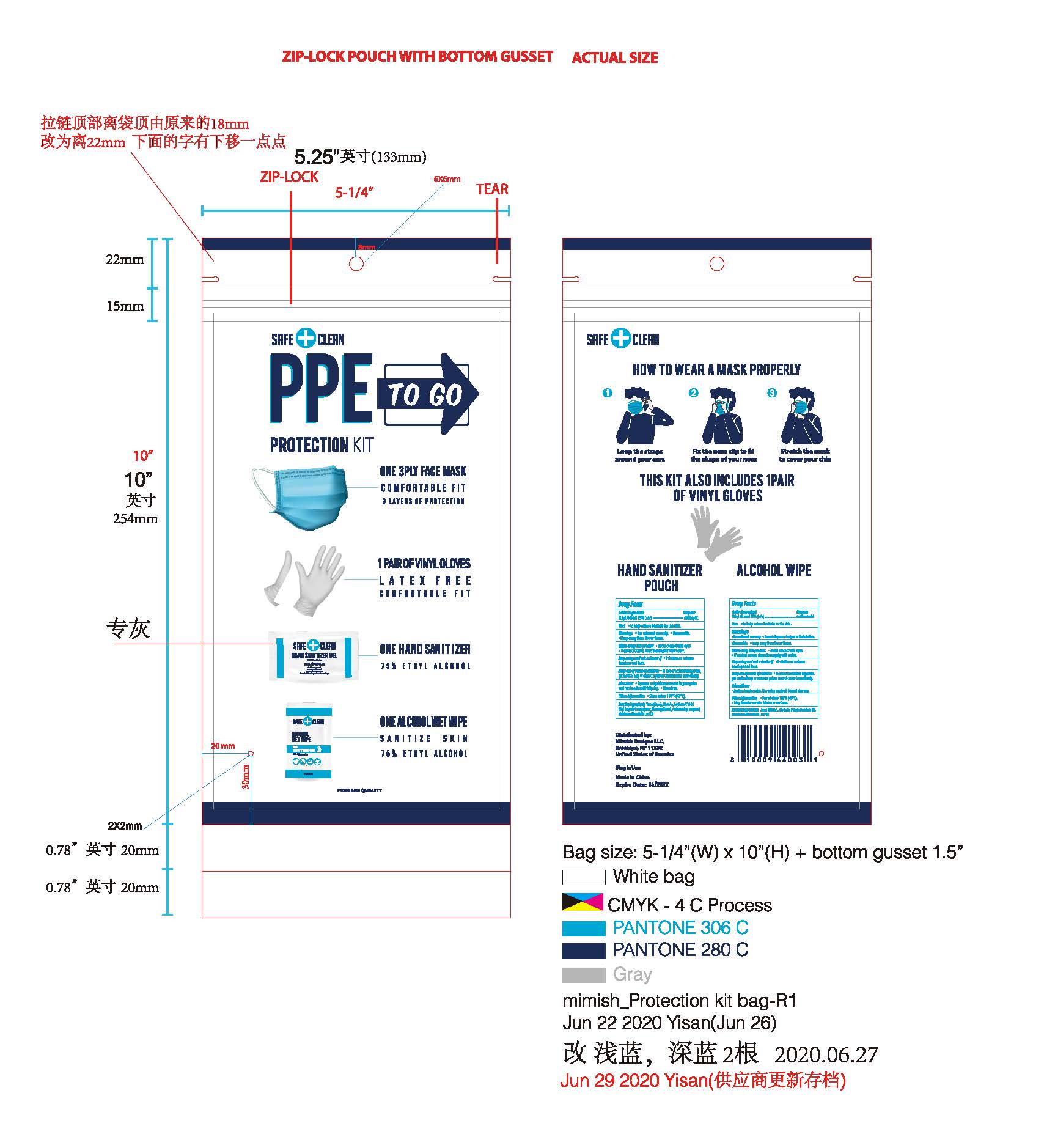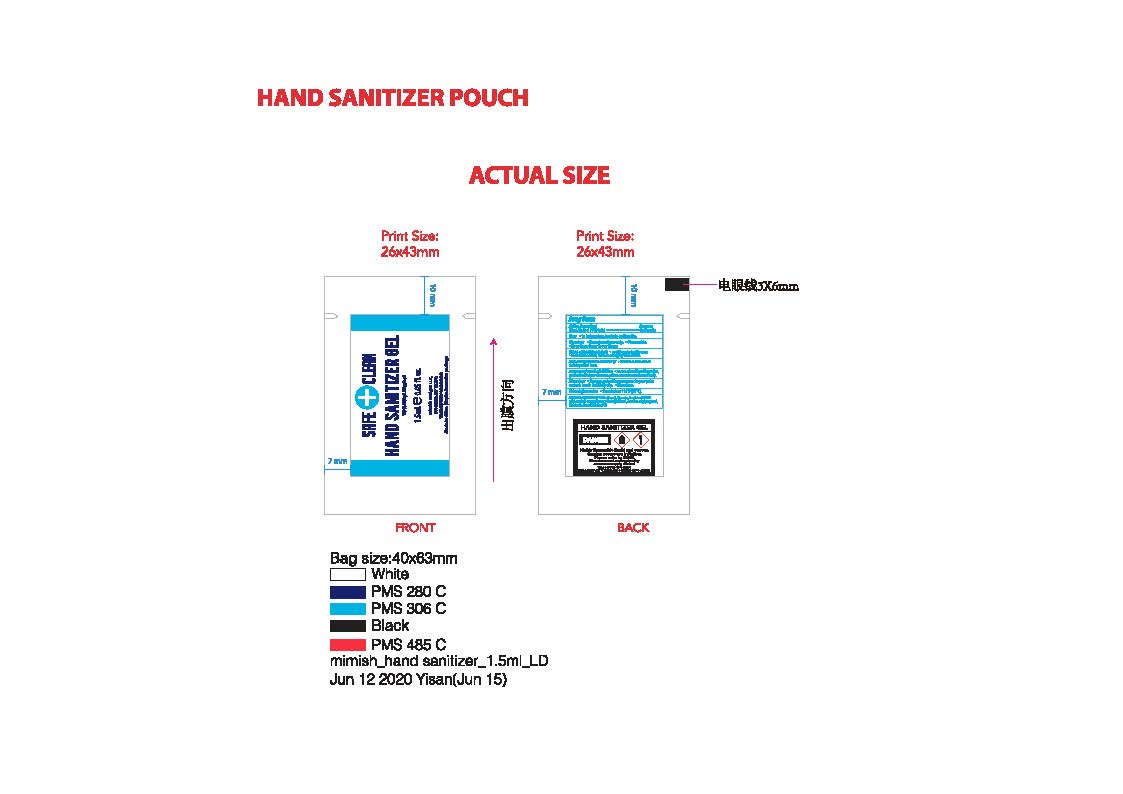 DRUG LABEL: Safe Clean Protection Kit
NDC: 79312-103 | Form: KIT | Route: TOPICAL
Manufacturer: Mimish Designs, LLC
Category: otc | Type: HUMAN OTC DRUG LABEL
Date: 20200709

ACTIVE INGREDIENTS: ALCOHOL 1.125 mL/1.5 mL; ALCOHOL 0.75 mL/1 1
INACTIVE INGREDIENTS: PHENOXYETHANOL; AMINOMETHYL PROPANEDIOL; WATER; MELALEUCA ALTERNIFOLIA LEAF; GLYCERIN; (C10-C30)ALKYL METHACRYLATE ESTER; WATER; GLYCERIN; POLYQUATERNIUM 37 (200 MPA.S); MELALEUCA ALTERNIFOLIA LEAF

Safe+Clean Protection Kit

Active Ingredient

Ethyl Alcohol 75%

Purpose

Antiseptic

Uses

To help reduce bacteria on skin.

Warnings

For External Use only. Flammable. Keep away from heat or flame.

When using this product

Avoid contact with eyes. If contact occurs, rinse thoroughly with water.

Stop use and ask a doctor.

If irritation or redness develops and last.

Keep out of reach of children.

In case of accidental ingestion, get medical help or contact a Poison Control Center immediately.

Directions

Squeeze a significant amount in your palm and rub hands until fully dry. Rinse free

Other Information

Store below 110F (43C)

Inactive Ingredients

Water (Aqua), Glycerin, Acrylates/C10-30 Alkyl Acrylate Crosspolymer, Phenoxyethanol, Aminomethyl propanol, Melaleuca Alternifolia Leaf Oil.